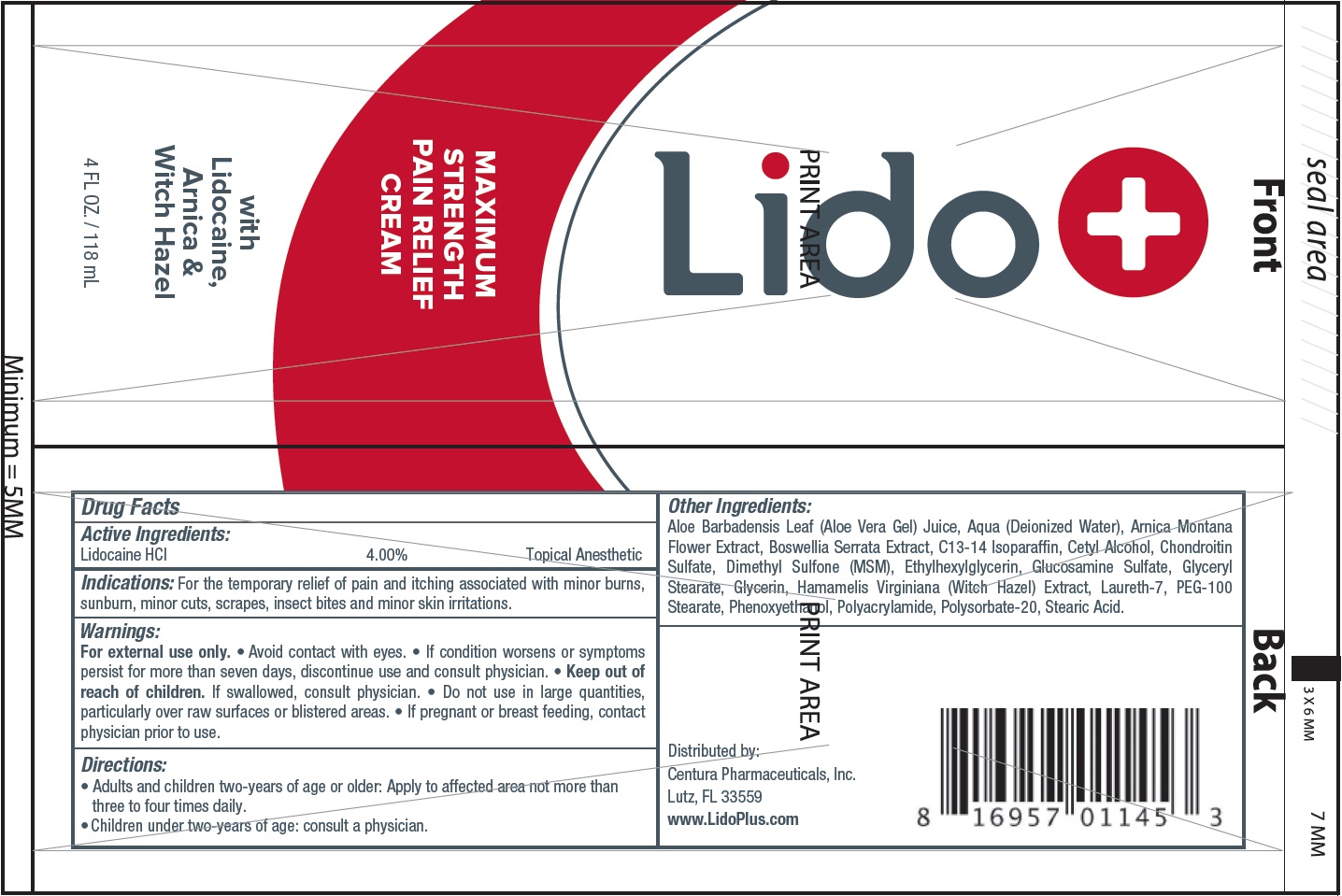 DRUG LABEL: LidoPlus Pain Relief
NDC: 70372-723 | Form: CREAM
Manufacturer: Centura Pharmaceuticals, Inc
Category: otc | Type: HUMAN OTC DRUG LABEL
Date: 20260112

ACTIVE INGREDIENTS: LIDOCAINE HYDROCHLORIDE 40 mg/1 mL
INACTIVE INGREDIENTS: ALOE VERA LEAF; WATER; ARNICA MONTANA FLOWER; INDIAN FRANKINCENSE; C13-14 ISOPARAFFIN; CETYL ALCOHOL; ETHYLHEXYLGLYCERIN; GLUCOSAMINE SULFATE; GLYCERYL MONOSTEARATE; GLYCERIN; HAMAMELIS VIRGINIANA TOP; LAURETH-7; PEG-100 STEARATE; PHENOXYETHANOL; POLYSORBATE 20; STEARIC ACID

LidoPlus Pain Relief Cream

Active Ingredients:

Lidocaine HCl 4.00%

PURPOSE

Topical Anesthetic

Indications:

For the temporary relief of pain and itching associated with minor burns, sunburn, minor cuts, scrapes, insect bites and minor skin irritations.

Warnings:

For external use only.

• Avoid contact with eyes. • If condition worsens or symptoms persist for more than seven days, discontinue use and consult physician.

Keep out of reach of children.

If swallowed, consult physician.

Do not use

in large quantities, particularly over raw surfaces or blistered areas.

If pregnant or breast feeding,

contact physician prior to use.

Directions:

• Adults and children two-years of age or older: Apply to affected area not more than three to four times daily.

• Children under two-years of age: consult a physician.

Other Ingredients:

Aloe Barbadensis Leaf (Aloe Vera Gel) Juice, Aqua (Deionized Water), Arnica Montana Flower Extract, Boswellia Serrata Extract, C13-14 Isoparaffin, Cetyl Alcohol, Chondroitin Sulfate, Dimethyl Sulfone (MSM), Ethylhexylglycerin, Glucosamine Sulfate, Glyceryl Stearate, Glycerin, Hamamelis Virginiana (Witch Hazel) Extract, Laureth-7, PEG-100 Stearate, Phenoxyethanol, Polyacrylamide, Polysorbate-20, Stearic Acid.